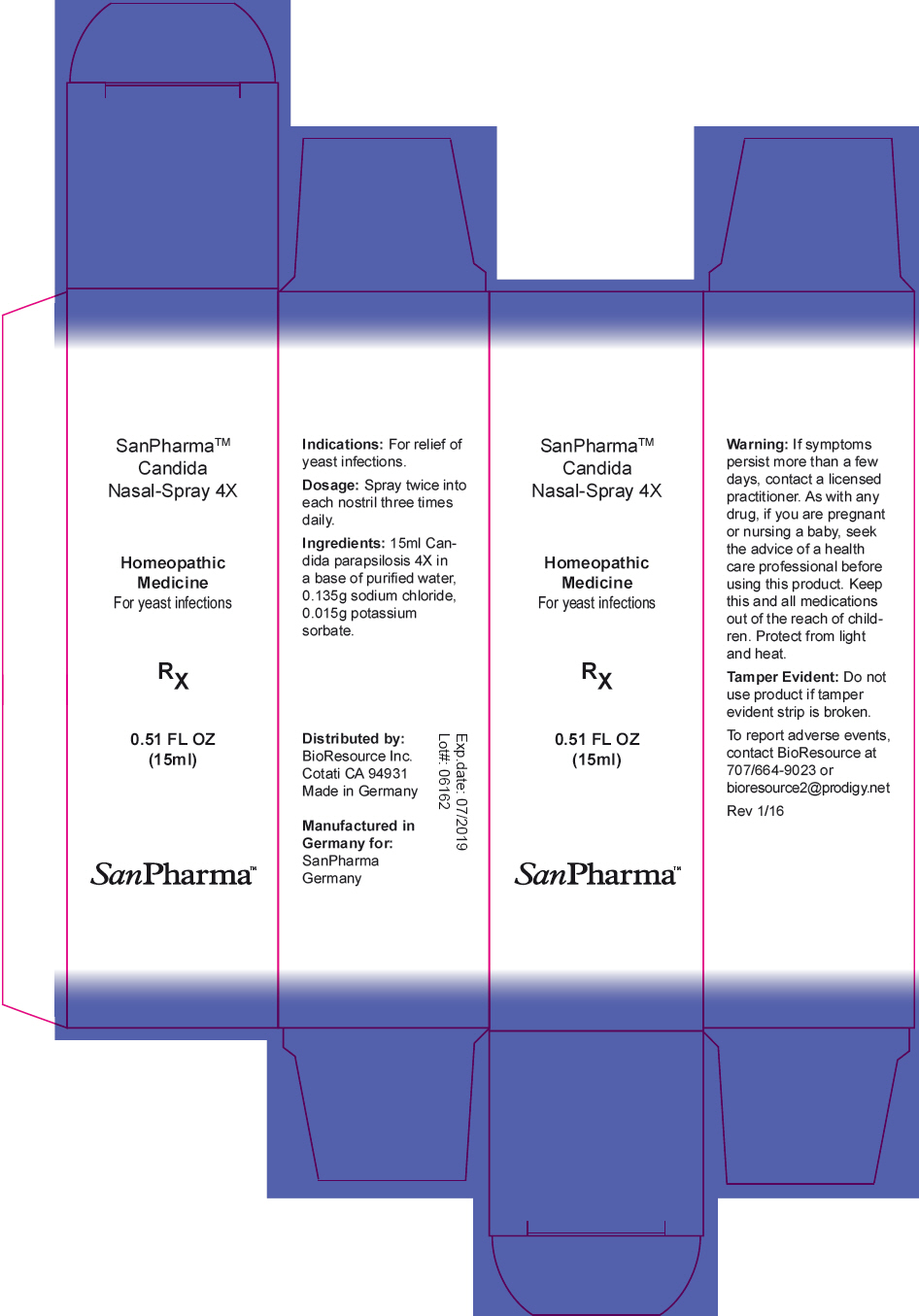 DRUG LABEL: Candida
NDC: 54256-099 | Form: SPRAY
Manufacturer: BioResource Inc.
Category: homeopathic | Type: HUMAN OTC DRUG LABEL
Date: 20160902

ACTIVE INGREDIENTS: Candida parapsilosis 4 [hp_X]/15 mL
INACTIVE INGREDIENTS: Water; Sodium chloride; Potassium sorbate

Candida Nasal Spray 4X

Indications

PURPOSE

For relief of yeast infections.

Dosage

Spray twice into each nostril three times daily.

Ingredients

INACTIVE INGREDIENT

15ml Candida parapsilosis 4X in a base of purified water, 0.135g sodium chloride, 0.015g potassium sorbate.

Warning

If symptoms persist more than a few days, contact a licensed practitioner. As with any drug, if you are pregnant or nursing a baby, seek the advice of a health care professional before using this product.

KEEP OUT OF REACH OF CHILDREN

Keep this and all medications out of the reach of children. Protect from light and heat.

Tamper Evident

Do not use product if tamper evident strip is broken.

QUESTIONS

To report adverse events, contact BioResource at 707/664-9023 or bioresource2@prodigy.net

Distributed by:
BioResource Inc.
Cotati CA 94931

PRINCIPAL DISPLAY PANEL - 15 ml Bottle Box

SanPharma™
Candida
Nasal-Spray 4X

Homeopathic
Medicine
For yeast infections

RX

0.51 FL OZ
(15ml)

San Pharma™